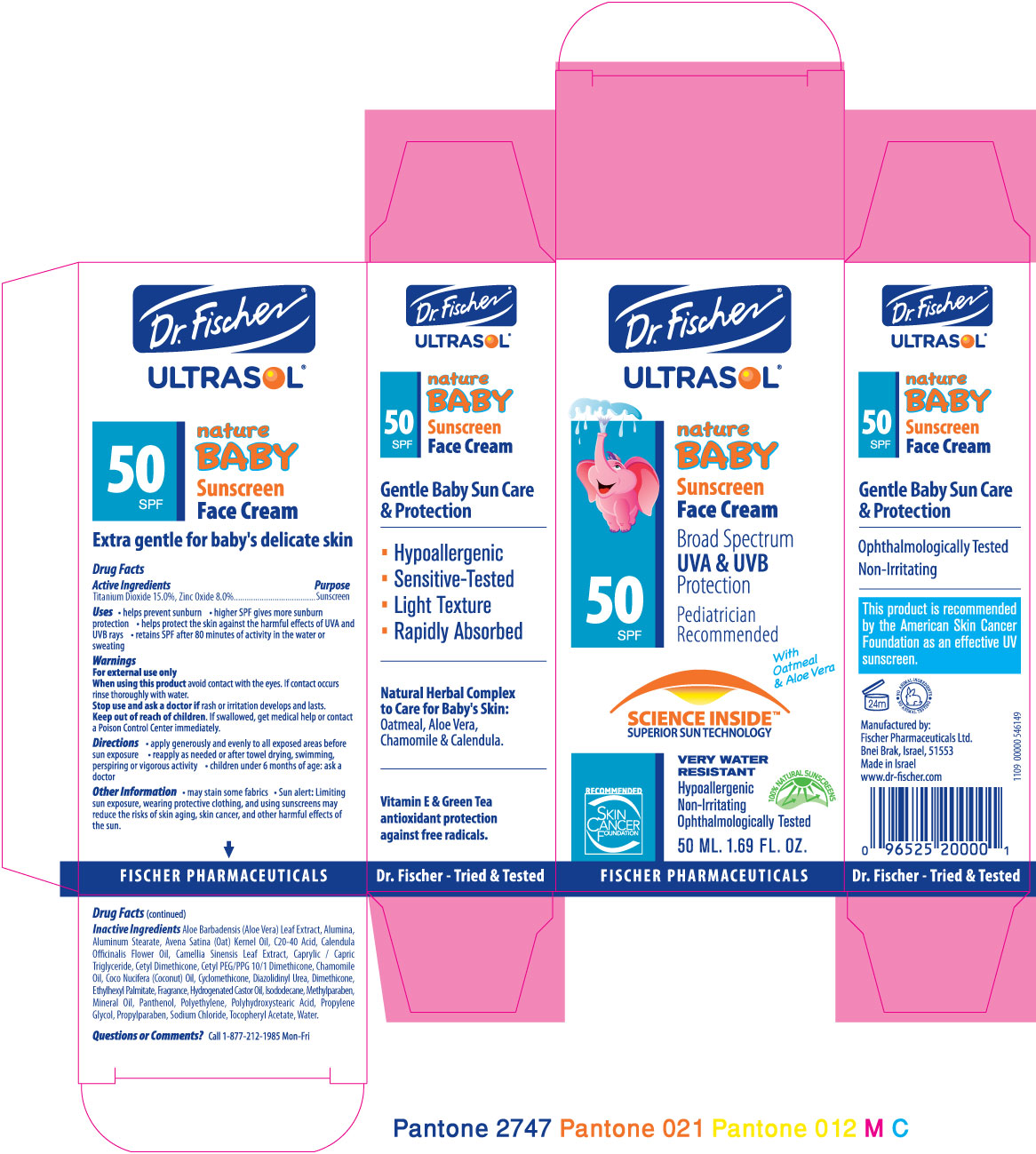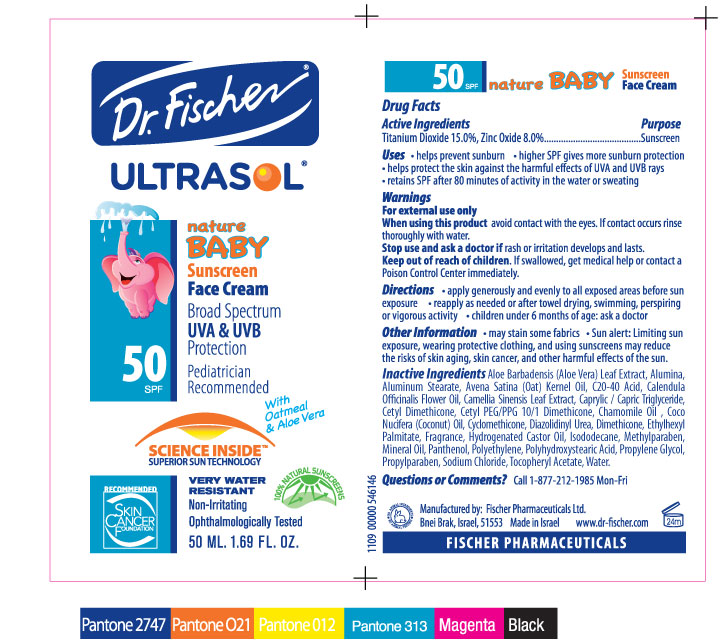 DRUG LABEL: ULTRASOL
NDC: 59886-304 | Form: CREAM
Manufacturer: Fischer Pharmaceuticals Ltd
Category: otc | Type: HUMAN OTC DRUG LABEL
Date: 20100509

ACTIVE INGREDIENTS: Titanium Dioxide 15 g/100 g; Zinc Oxide 8 g/100 g
INACTIVE INGREDIENTS: ALUMINUM OXIDE; Aluminum Stearate ; Coconut Oil ; Methylparaben; Panthenol; Propylene Glycol; Sodium Chloride ; ALPHA-TOCOPHEROL ACETATE; Water

Dr. Fischer ULTRASOL nature BABY Sunscreen Face Cream SPF50

Drug Facts

Active Ingredients Purpose
Titanium Dioxide 15.0%, Zinc Oxide 8.0%.......................................... Sunscreen

Uses

• helps prevent sunburn • higher SPF gives more sunburn protection
• helps protect the skin against the harmful effects of UVA and UVB rays
• retains SPF after 80 minutes of activity in the water or sweating

Warnings

For external use only

When using this product

avoid contact with the eyes. If contact occurs rinse
thoroughly with water.

Stop use and ask a doctor if

rash or irritation develops and lasts.

Keep out of reach of children.

If swallowed, get medical help or contact
a Poison Control Center immediately.

Directions

• apply generously and evenly to all exposed areas before sun exposure
• reapply as needed or after towel drying, swimming, perspiring or vigorous activity
• children under 6 months of age: ask a doctor

Other Information

• may stain some fabrics
• Sun alert: Limiting sun exposure, wearing protective clothing, and using
sunscreens may reduce the risks of skin aging, skin cancer, and other harmful
effects of the sun.

Inactive Ingredients

Aloe Barbadensis (Aloe Vera) Leaf Extract, Alumina,
Aluminum Stearate, Avena Satina (Oat) Kernel Oil, C20-40 Acid, Calendula
Officinalis Flower Oil, Camellia Sinensis Leaf Extract, Caprylic / Capric Triglyceride,
Cetyl Dimethicone, Cetyl PEG/PPG 10/1 Dimethicone, Chamomile Oil, Coco
Nucifera (Coconut) Oil, Cyclomethicone, Diazolidinyl Urea, Dimethicone, Ethylhexyl
Palmitate, Fragrance, Hydrogenated Castor Oil, Isododecane, Methylparaben,
Mineral Oil, Panthenol, Polyethylene, Polyhydroxystearic Acid, Propylene Glycol,
Propylparaben, Sodium Chloride, Tocopheryl Acetate, Water.

Questions or Comments?

Call 1-877-212-1985 Mon-Fri

PACKAGE LABEL

Dr. Fischer ULTRASOL

nature BABY Sunscreen Face Cream SPF50

Broad Spectrum UVA and UVB Protection

Pediatrician Recommended

SCIENCE INSIDETM SUPERIOR SUN TECHNOLOGY

VERY WATER RESISTANT

Non-Irritating

Ophthalmologically Tested

RECOMMENDED SKIN CANCER FOUNDATION

This product is recommended by the American Skin Cancer Foundation as an effective UV sunscreen

Extra gentle for baby's delicate skin

Gentle Baby Sun Care and Protection

Hypoallergenic

Sensitive-Tested

Light Texture

Rapidly Absorbed

Natural Herbal Complex to Care for Baby's Skin: Oatmeal, Aloe Vera,

Chamomile and Calendula

Vitamin E and Green Tea antioxidant protection against free radicals

50 ML. 1.69 FL. OZ.

100% NATURAL SUNSCREENS

Manufactured by:

Fischer Pharmaceuticals Ltd.

Bnei Brak, Israel, 51553

Made in Israel

www.dr-fischer.com

Fischer Pharmaceuticals

Dr. Fischer - Tried and Tested

24m

NO ANIMAL TESTING NO ANIMAL INGREDIENTS